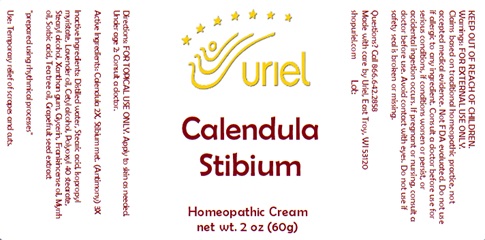 DRUG LABEL: Calendula Stibium
NDC: 48951-3015 | Form: CREAM
Manufacturer: Uriel Pharmacy Inc.
Category: homeopathic | Type: HUMAN OTC DRUG LABEL
Date: 20240115

ACTIVE INGREDIENTS: CALENDULA OFFICINALIS FLOWERING TOP 2 [hp_X]/1 g; ANTIMONY 3 [hp_X]/1 g
INACTIVE INGREDIENTS: STEARIC ACID; ISOPROPYL MYRISTATE; LAVENDER OIL; CETYL ALCOHOL; POLYOXYL 40 STEARATE; STEARYL ALCOHOL; XANTHAN GUM; GLYCERIN; SORBIC ACID; FRANKINCENSE OIL; MYRRH OIL; CITRUS PARADISI SEED; WATER; TEA TREE OIL

Calendula Stibium

INDICATIONS AND USAGE

Directions: FOR TOPICAL USE ONLY.

DOSAGE AND ADMINISTRATION

Apply to skin as needed. Under age 2: Consult a doctor.

Active Ingredients: Calendula 2X, Stibium met. (Antimony) 3X

INACTIVE INGREDIENT

Inactive Ingredients: Distilled water, Stearic acid, Isopropyl myristate, Lavender oil, Cetyl alcohol, Polyoxyl 40 stearate, Stearyl alcohol, Xanthan gum, Glycerin, Frankincense oil, Myrrh oil, Sorbic acid, Tea tree oil, Grapefruit seed extract

"prepared using rhythmical processes"

PURPOSE

Use: Temporary relief of scrapes and cuts.

KEEP OUT OF REACH OF CHILDREN.

WARNINGS

Warnings: FOR EXTERNAL USE ONLY. Do not use if allergic to any ingredient. Consult a doctor before use for serious conditions, if conditions worsen or persist, or accidental ingestion occurs. If pregnant or nursing, consult a doctor before use. Avoid contact with eyes. Do not use if safety seal is broken or missing.

QUESTIONS

Questions? Call 866.642.2858 Made with care by Uriel, East Troy, WI 53120 shopuriel.com